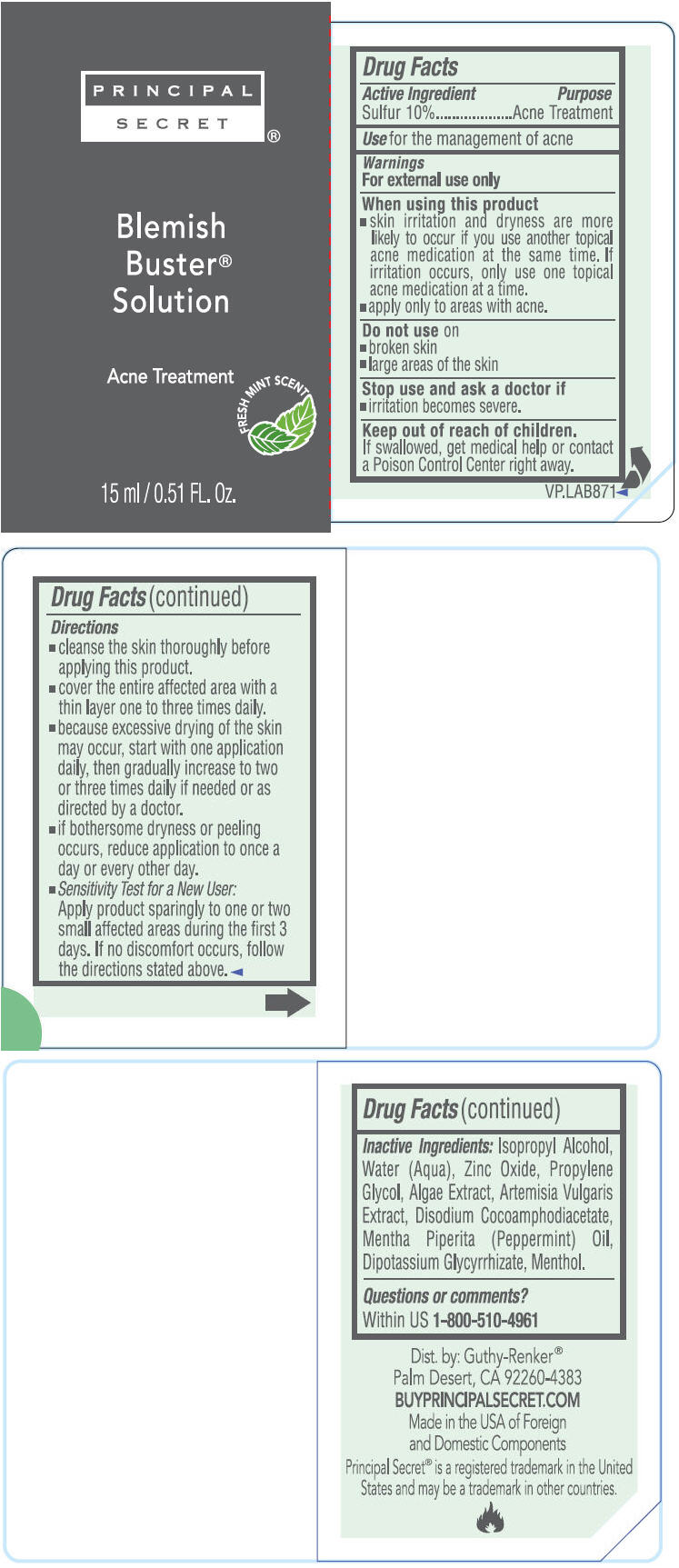 DRUG LABEL: Blemish Buster Solution Acne Treatment
NDC: 70605-018 | Form: CREAM
Manufacturer: Guthy-Renker LLC
Category: otc | Type: HUMAN OTC DRUG LABEL
Date: 20251201

ACTIVE INGREDIENTS: SULFUR 10 mg/100 mL
INACTIVE INGREDIENTS: ISOPROPYL ALCOHOL; WATER; SHEA BUTTER; ZINC OXIDE; PROPYLENE GLYCOL; PEPPERMINT OIL; GLYCYRRHIZINATE DIPOTASSIUM; MENTHOL, UNSPECIFIED FORM

Blemish Buster® Solution Acne Treatment

Active ingredient

Sulfur 10%

Purpose

Acne Treatment

Use

For the management of acne

Warnings

For external use only

When using this product

- skin irritation and dryness are more likely to occur if you use another topical acne medication at the same time. If irritation occurs, only use one topical acne medication at a time.
- apply only to areas with acne.

Do not use on

- broken skin
- large areas of the skin

Stop use and ask a doctor if

- irritation becomes severe.

Keep out of reach of children.

If swallowed, get medical help or contact a Poison Control right away.

Directions

- cleanse the skin thoroughly before applying this product.
- cover the entire affected area with one to three times daily.
- because excessive drying of the skin may occur, start with one application daily, then gradually increase to two or three times daily if needed or as directed by a doctor.
- if bothersome dryness or peeling occurs, reduce application to once a day or every other day.

Sensitivity Test for a New User

Apply product sparingly to one or two small affected areas during the first 3 days. If no discomfort occurs, follow the directions stated above

Inactive ingredients

Isopropyl Alcohol, Water, Zinc Oxide, Propylene Glycol, Algae Extract, Artemisia Vulgaris Extract, Disodium Cocoamphodiacetate, Mentha Piperita (Peppermint) Oil, Dipotassium Glycyrrhizate, Menthol.

Questions or comments?

Within US 1-800-510-4961

Dist. by: Guthy-Renker®
Palm Desert, CA 92260-4383

PRINCIPAL DISPLAY PANEL - 15 ml Bottle Label

PRINCIPAL
SECRET®

Blemish
Buster®
Solution

Acne Treatment

FRESH MINT SCENT

15 ml / 0.51 FL. Oz.